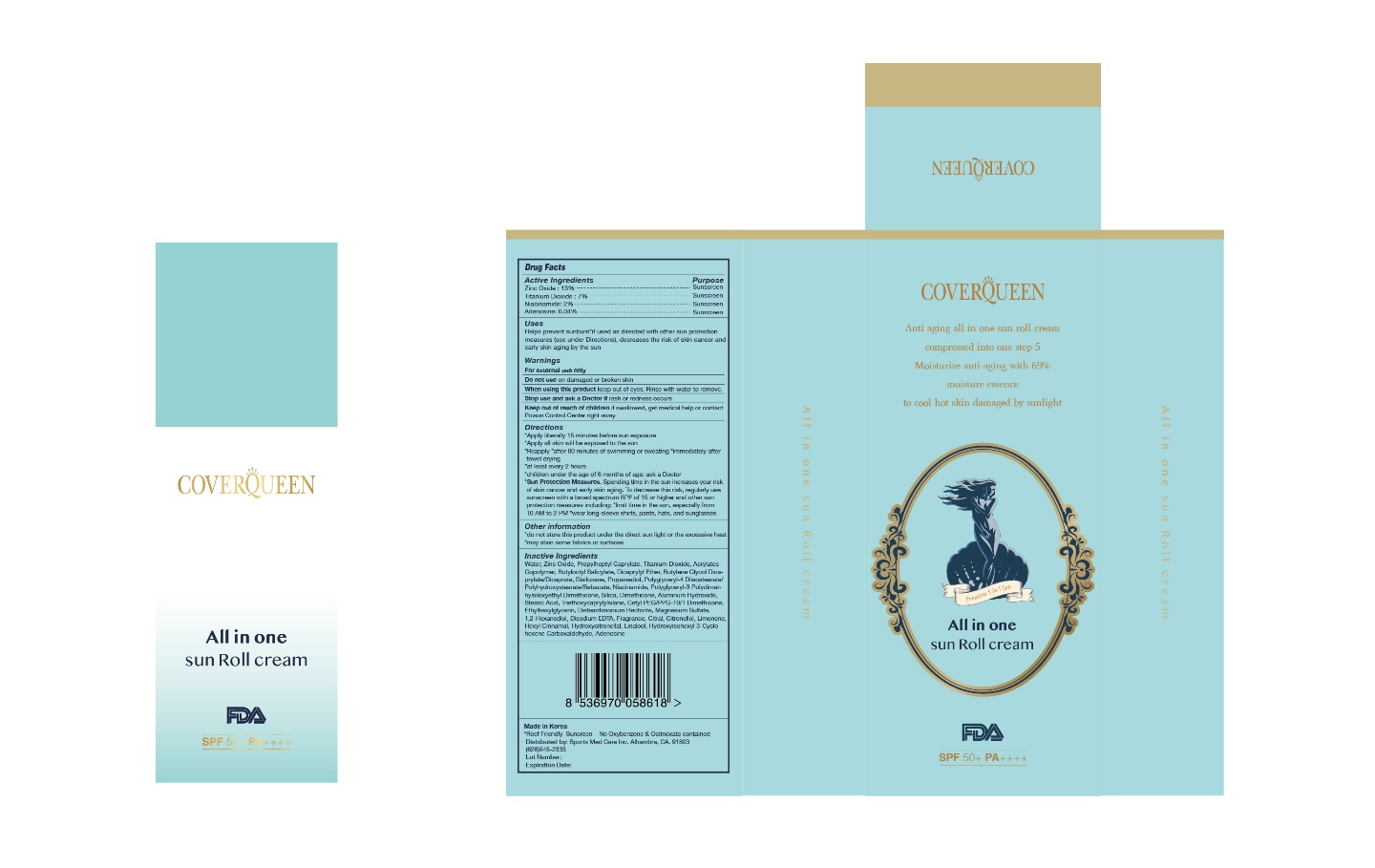 DRUG LABEL: COVERQUEEN All in one sun roll
NDC: 73793-0013 | Form: CREAM
Manufacturer: SKINFARM
Category: otc | Type: HUMAN OTC DRUG LABEL
Date: 20210325

ACTIVE INGREDIENTS: ADENOSINE 0.04 g/100 g; NIACINAMIDE 2 g/100 g; TITANIUM DIOXIDE 7 g/100 g; ZINC OXIDE 13 g/100 g
INACTIVE INGREDIENTS: WATER; DIMETHICONE

Drug Facts

ACTIVE INGREDIENT

Zinc Oxide, Titanium Dioxide, Niacinamide, Adenosine

INACTIVE INGREDIENT

Water, Propylheptyl Caprylate, Acrylates Copolymer, Butyloctyl Salicylate, Dicaprylyl Ether, Butylene Glycol, Dicaprylate/Dicaprate, Disiloxane, Propanediol, Polyglyceryl-4 Diisostearate/Polyhydroxystearate/Sebacate, Polyglyceryl-3 Polydimethylsiloxyethyl Dimethicone, Silica, Dimethicone, Aluminum Hydroxide, Stearic Acid, Triethoxycaprylylsilane, Cetyl PEG/PPG-10/1 Dimethicone, Ethylhexylglycerin, Disteardimonium Hectorite, Magnesium Sulfate, 1,2-Hexanediol, Disodium EDTA, Fragrance, Citral, Citronellol, Limonene, Hexyl Cinnamal, Hydroxycitronellal, Linalool, Hydroxyisohexyl 3-Cyclohexene Carboxaldehyde,

PURPOSE

Helps prevent sunburn*if used as directed with other sun protection measures (see under Directions), decreases the risk of skin cancer and early skin aging by the sun

KEEP OUT OF REACH OF THE CHILDREN

Directions

*Apply liberally 15 minutes before sun exposure

*Apply all skin will be exposed to the sun

*Reapply *after 80 minutes of swimming or sweating *immediately after towel drying

*at least every 2 hours

*children under the age of 6 months of age: ask a Doctor

*Sun Protection Measures. Spending time in the sun increases your risk of skin cancer and early skin aging. To decrease this risk, regularly use sunscreen with a broad spectrum SPF of 15 or higher and other sun protection measures including: *limit time in the sun, especially from 10 AM to 2 PM *wear long-sleeve shirts, pants, hats, and sunglasses

Warnings

For external use only

Do not use on damaged or broken skin

When using this product keep out of eyes. Rinse with water to remove.

Stop use and ask a Doctor if rash or redness occurs

Keep out of reach of children if swallowed, get medical help or contact Poison Control Center right away

Other information

*do not store this product under the direct sun light or the excessive heat

*may stain some fabrics or surfaces

DOSAGE AND ADMINISTRATION

external use only